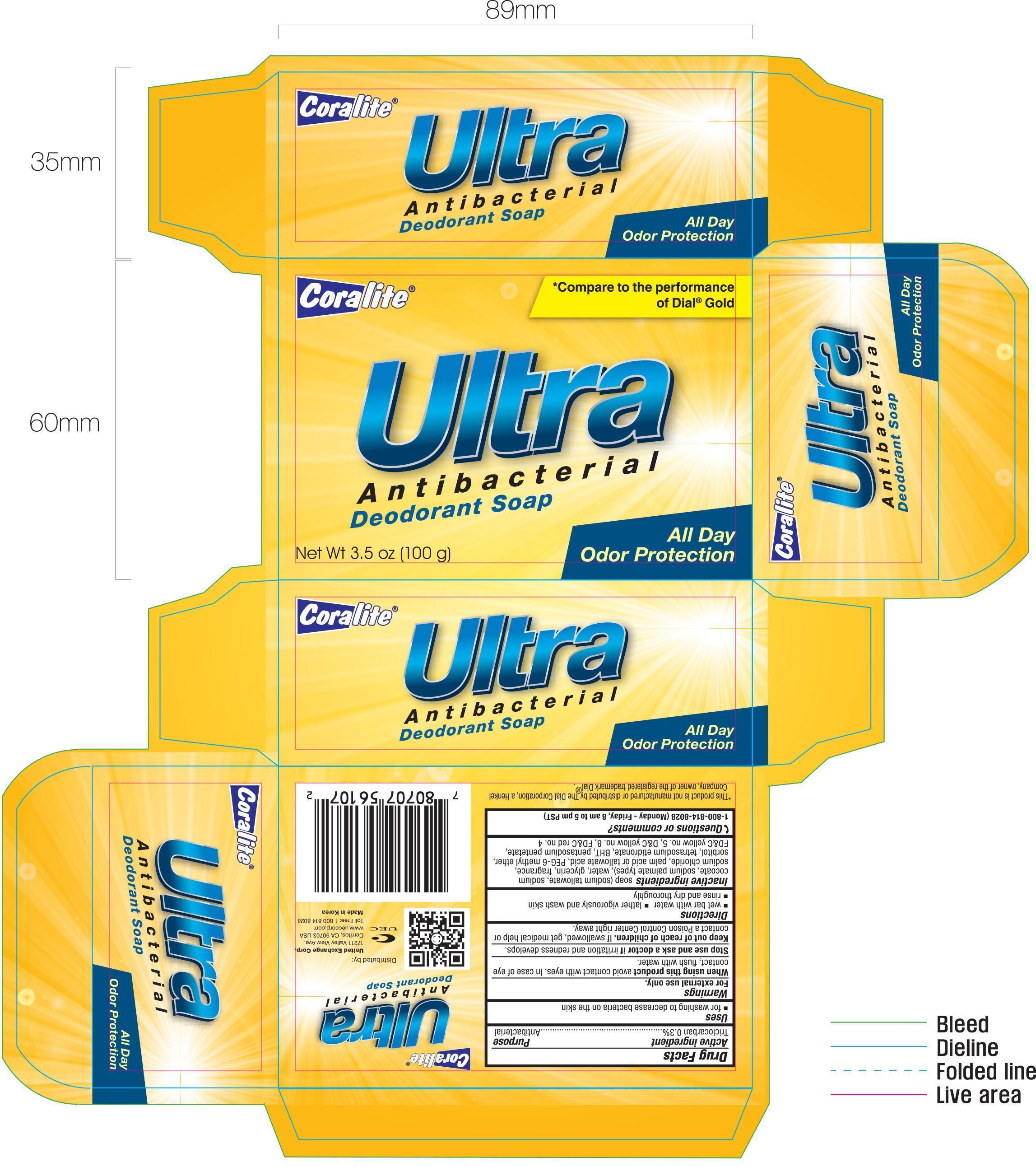 DRUG LABEL: Coralite Ultra Antibacterial Deodorant
                
NDC: 65923-807 | Form: SOAP
Manufacturer: United Exchange Corp
Category: otc | Type: HUMAN OTC DRUG LABEL
Date: 20140730

ACTIVE INGREDIENTS: TRICLOCARBAN 0.3 g/100 g
INACTIVE INGREDIENTS: SODIUM COCOATE; SODIUM PALMATE; WATER; GLYCERIN; SODIUM CHLORIDE; PALM ACID; PEG-6 METHYL ETHER; SORBITOL; PENTASODIUM PENTETATE; FD&C YELLOW NO. 5; D&C YELLOW NO. 8; FD&C RED NO. 4

Drug Facts

Active ingredient Purpose

Triclocarban 0.3%....................................................Antibacterial

Uses

- for washing to decrease bacteria on the skin

Warnings For external use only.

When using this product avoid contact with eyes. In case of eye contact, flush with water.

Stop use and ask a doctor if irritation and redness develops.

Keep out of reach of children. If swallowed, get medical help or contact a Poison Control Center right away.

Directions

- wet bar with water
- lather vigorously and wash skin
- rinse and dry thoroughly

INACTIVE INGREDIENT

Inactive ingredients soap (sodium tallowate, sodium cocoate, sodium palmate types), water, glycerin, fragrance, sodium chlroide, palm acid or tallowate acid, PEG-6 methyl ether, sorbitol, tetrasdoium etidronate, BHT, pentasodium pentetate, FD&C yellow no. 5, D&C yellow no. 8, FD&C red no. 4

DOSAGE AND ADMINISTRATION

Distributed By:

United Exchange Corp.

17211 Valley View Ave.

Cerritos, CA 90703 USA

Made in Korea